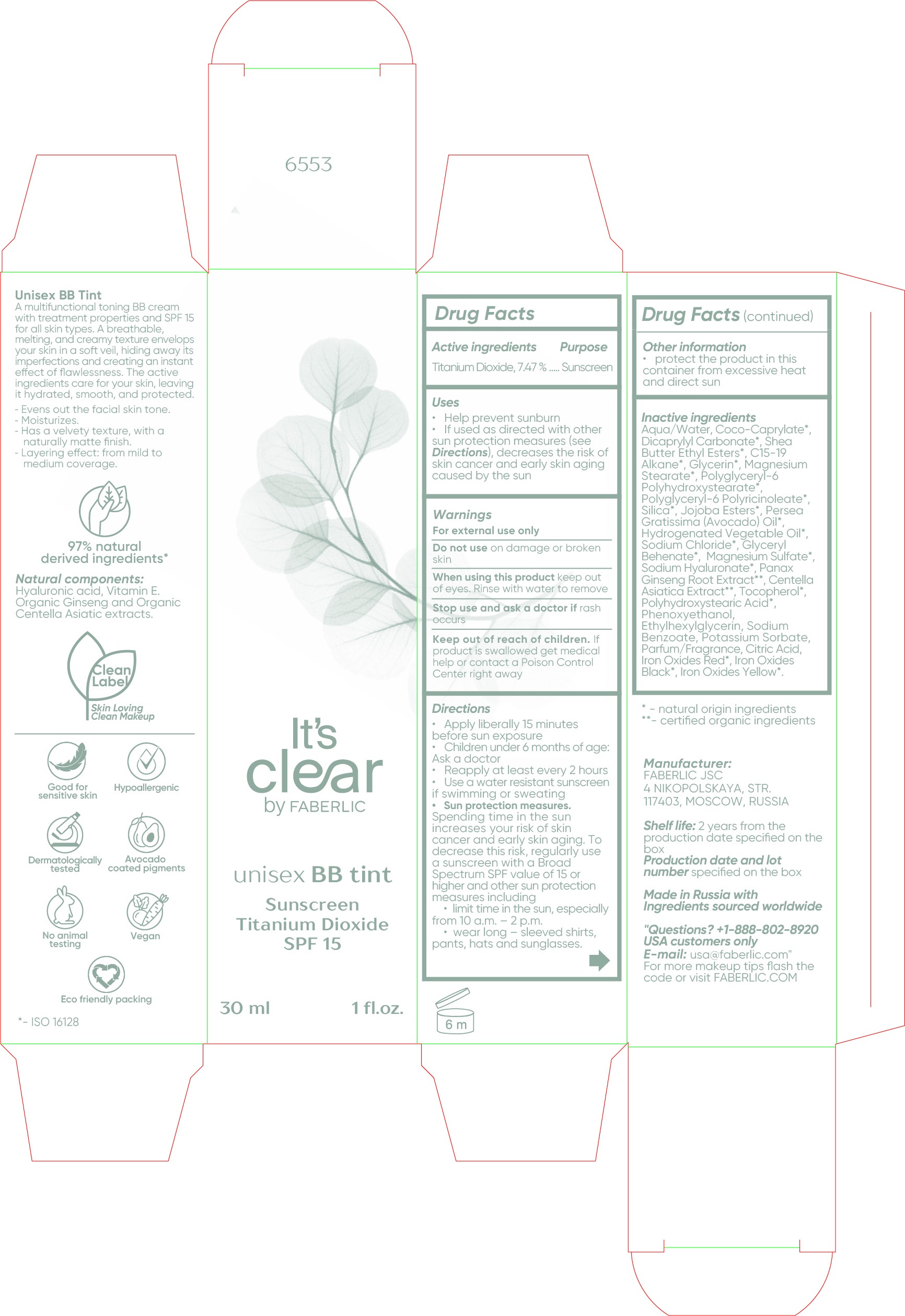 DRUG LABEL: Unisex BB Tint- It s Clear - 6553
NDC: 82063-6553 | Form: CREAM
Manufacturer: Faberlic Joint Stock Company
Category: otc | Type: HUMAN OTC DRUG LABEL
Date: 20211226

ACTIVE INGREDIENTS: TITANIUM DIOXIDE 74.7 mg/1 mL
INACTIVE INGREDIENTS: WATER; COCO-CAPRYLATE; DICAPRYLYL CARBONATE; SHEA BUTTER ETHYL ESTERS; C15-19 ALKANE; GLYCERIN; MAGNESIUM STEARATE; POLYGLYCERYL-6 POLYRICINOLEATE; SILICON DIOXIDE; AVOCADO OIL; SODIUM CHLORIDE; MAGNESIUM SULFATE, UNSPECIFIED FORM; HYALURONATE SODIUM; ASIAN GINSENG; CENTELLA ASIATICA TRITERPENOIDS; TOCOPHEROL; PHENOXYETHANOL; ETHYLHEXYLGLYCERIN; SODIUM BENZOATE; POTASSIUM SORBATE; CITRIC ACID MONOHYDRATE; FERRIC OXIDE RED; FERROSOFERRIC OXIDE; FERRIC OXIDE YELLOW

Unisex BB Tint- It's Clear - 6553

Active ingredients

Titanium Dioxide, 7.47%

Purpose

Sunscreen

Uses

- Helps prevent sunburn
- If used as directed with other sun protection measures (see Directions), decreases the risk of skin cancer and early skin aging caused by the sun

Warnings

For external use only

Do not use

on damage or broken skin

When using this product

keep out of eyes. Rinse with water to remove

Stop use and ask a doctor if

rash occurs

Keep out of reach of children.

If product is swallowed get medical help or contact a Poison Control Center right away

Directions

- Apply liberally 15 minutes before sun exposure
- Children undre 6 months of age: Ask a doctor
- Reapply at least every 2 hours
- Use a water resistant sunscreen if swimming or sweating
- Sun protection measures.
- Spending time in the sun increases your risk of skin cancer and early skin aging. To decrease this risk, reguarly use a sunscreen with a Broad Spectrum SPF value of 15 or higher and other sun protection measures including
- limit time in the sun, especially from 10 a.m. - 2 p.m.
- wear long - sleeved shirts, pants, hats and sunglasses.

Other information

- protect the product in this container from excessive heat and direct sun

Inactive ingredients

Aqua/Water, Coco-Caprylate*, Dicaprylyl Carbonate*, Shea Butter Ethyl Ester*, C15-19 Alkane*, Glycerin*, Magnesium Stearate*, Polyglyceryl-6 Polyhydroxystearate*, Polyglyceryl-6 Polyricinoleate*, Silica*, Jojoba Esters*, Persea Gratissima (Avocado) Oil*, Hydrogenated Vegetable Oil*, Sodium Chloride*, Glyceryl Behenate*, Magnesium Sulfate*, Sodium Hyaluronate*, Panax Ginseng Root Extract**, CentellaAsiatica Extract**, Tocopherol*, Polyhydroxystearic Acid*, Phenoxyethanol, Ethylhexylglycerin, Sodium Benzoate, Potassium Sorbate, Parfum/Fragrance, Citric Acid, Iron Oxides Red*, Iron Oxides Black, Iron Oxides Yellow*.